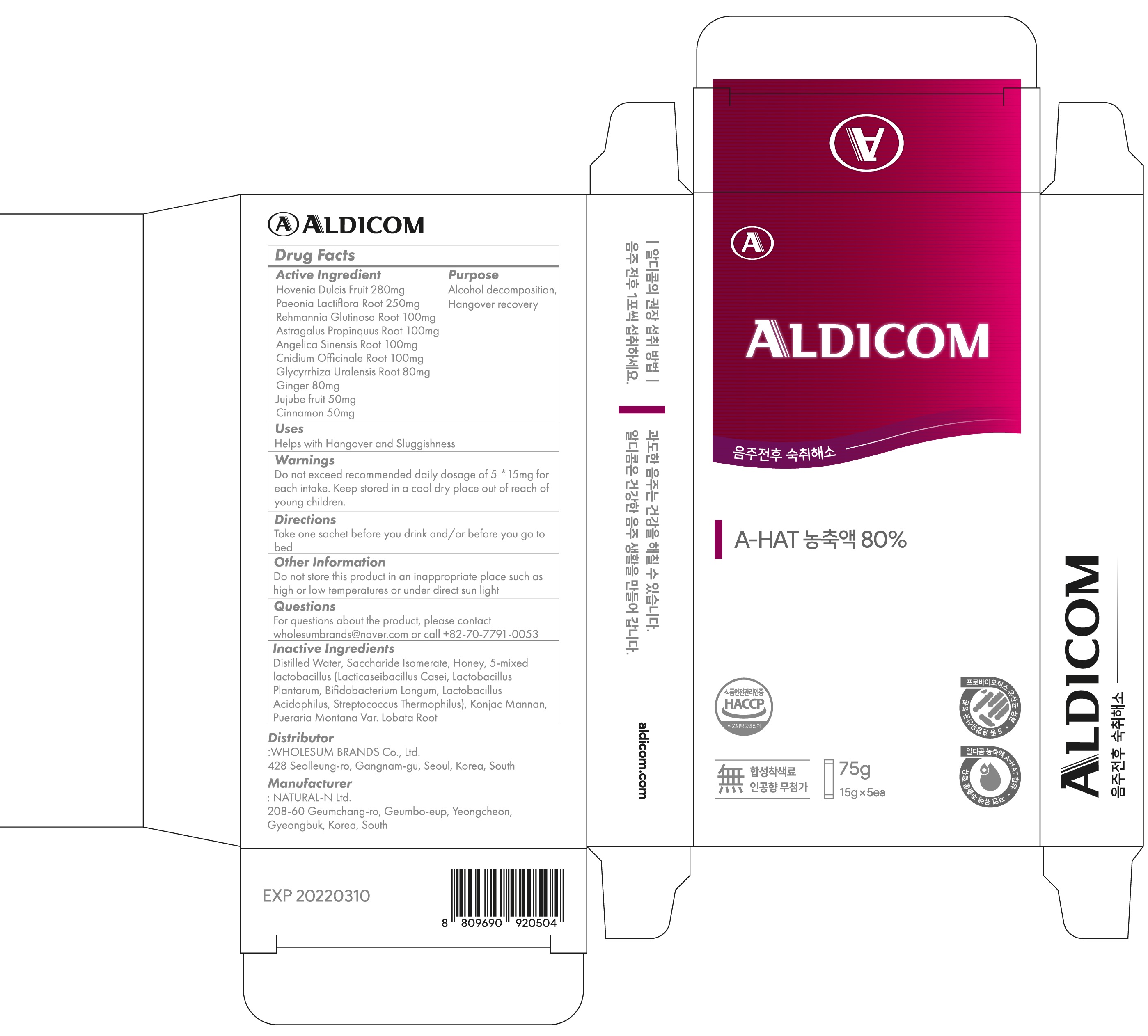 DRUG LABEL: ALDICOM
NDC: 82597-020 | Form: LIQUID
Manufacturer: Wholesum Brands Co., Ltd.
Category: otc | Type: HUMAN OTC DRUG LABEL
Date: 20240124

ACTIVE INGREDIENTS: Hovenia Dulcis Fruit 280 mg/15 g; Paeonia Lactiflora Root 250 mg/15 g; Rehmannia Glutinosa Root 100 mg/15 g; Astragalus Propinquus Root 100 mg/15 g; Angelica Sinensis Root 100 mg/15 g; Cnidium Officinale Root 100 mg/15 g; Glycyrrhiza Uralensis Root 80 mg/15 g; Ginger 80 mg/15 g; Jujube fruit 50 mg/15 g; Cinnamon 50 mg/15 g
INACTIVE INGREDIENTS: Water; HONEY

ACTIVE INGREDIENTS

Hovenia Dulcis Fruit 280mg
Paeonia Lactiflora Root 250mg
Rehmannia Glutinosa Root 100mg
Astragalus Propinquus Root 100mg
Angelica Sinensis Root 100mg
Cnidium Officinale Root 100mg
Glycyrrhiza Uralensis Root 80mg
Ginger 80mg
Jujube fruit 50mg
Cinnamon 50mg

INACTIVE INGREDIENTS

Distilled Water, Saccharide Isomerate, Honey, 5-mixed lactobacillus (Lacticaseibacillus Casei, Lactobacillus Plantarum, Bifidobacterium Longum, Lactobacillus Acidophilus, Streptococcus Thermophilus), Konjac Mannan, Pueraria Montana Var. Lobata Root

PURPOSE

Alcohol decomposition, Hangover recovery

WARNINGS

Do not exceed recommended daily dosage of 5 *15mg for each intake. Keep stored in a cool dry place out of reach of young children.

KEEP OUT OF REACH OF CHILDREN

Keep stored in a cool dry place out of reach of young children.

Uses

■ Helps with Hangover and Sluggishness

Directions

Take one sachet before you drink and/or before you go to bed

Other Information

Do not store this product in an inappropriate place such as high or low temperatures or under direct sun light

QUESTIONS

For questions about the product, please contact wholesumbrands@naver.com or call +82-70-7791-0053